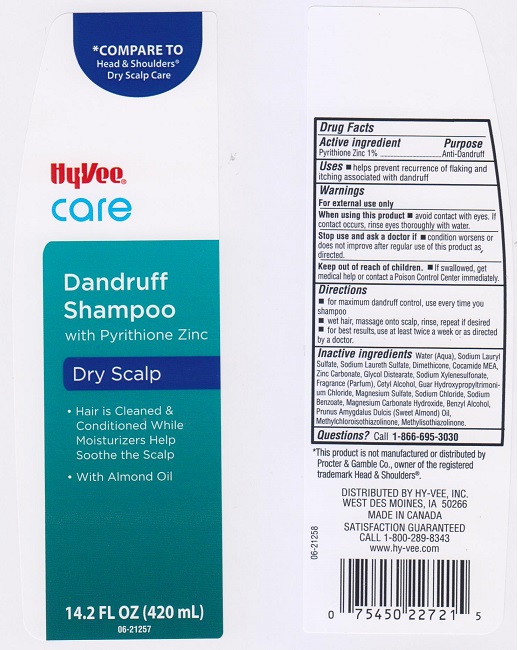 DRUG LABEL: Hyvee Care Dry Scalp Dandruff
NDC: 42507-429 | Form: SHAMPOO
Manufacturer: Hyvee Inc
Category: otc | Type: HUMAN OTC DRUG LABEL
Date: 20160614

ACTIVE INGREDIENTS: PYRITHIONE ZINC 10 mg/1 mL
INACTIVE INGREDIENTS: WATER; SODIUM LAURYL SULFATE; SODIUM LAURETH SULFATE; DIMETHICONE; COCO MONOETHANOLAMIDE; ZINC CARBONATE; GLYCOL DISTEARATE; SODIUM XYLENESULFONATE; CETYL ALCOHOL; GUAR HYDROXYPROPYLTRIMONIUM CHLORIDE (1.7 SUBSTITUENTS PER SACCHARIDE); MAGNESIUM SULFATE; SODIUM CHLORIDE; SODIUM BENZOATE; MAGNESIUM CARBONATE HYDROXIDE; BENZYL ALCOHOL; ALMOND OIL; METHYLCHLOROISOTHIAZOLINONE; METHYLISOTHIAZOLINONE

DRUG FACTS

Active ingredient

Pyrithione Zinc 1%

Purpose

Anti-dandruff

Uses

- helps prevent recurrence of flaking and itching associated with dandruff.

Warnings

For external use only.

When using this product

- avoid contact with eyes. If contact occurs, rinse eyes thoroughly with water.

Stop use and ask a doctor if

- condition worsens or does not improve after regular use of this product as directed.

Keep out of reach of children.

- If swallowed, get medical help or contact a Poison Control Center immediately.

Directions

- for maximum dandruff control, use every time you shampoo.
- wet hair, massage onto scalp, rinse, repeat if desired.
- for best results, use at least twice a week or as directed by a doctor.

Inactive ingredients

Water (Aqua), Sodium Lauryl Sulfate, Sodium Laureth Sulfate, Dimethicone, Cocamide MEA, Zinc Carbonate, Glycol Distearate, Sodium Xylenesulfonate, Fragrance (Parfum), Cetyl Alcohol, Guar Hydroxypropyltrimonium Chloride, Magnesium Sulfate, Sodium Chloride, Sodium Benzoate, Magnesium Carbonate Hydroxide, Benzyl Alcohol, Prunus Amygdalus Dulcis (Sweet Almond) Oil, Methylchloroisothiazolinone, Methylisothiazolinone.

Questions?

Call 1-866-695-3030